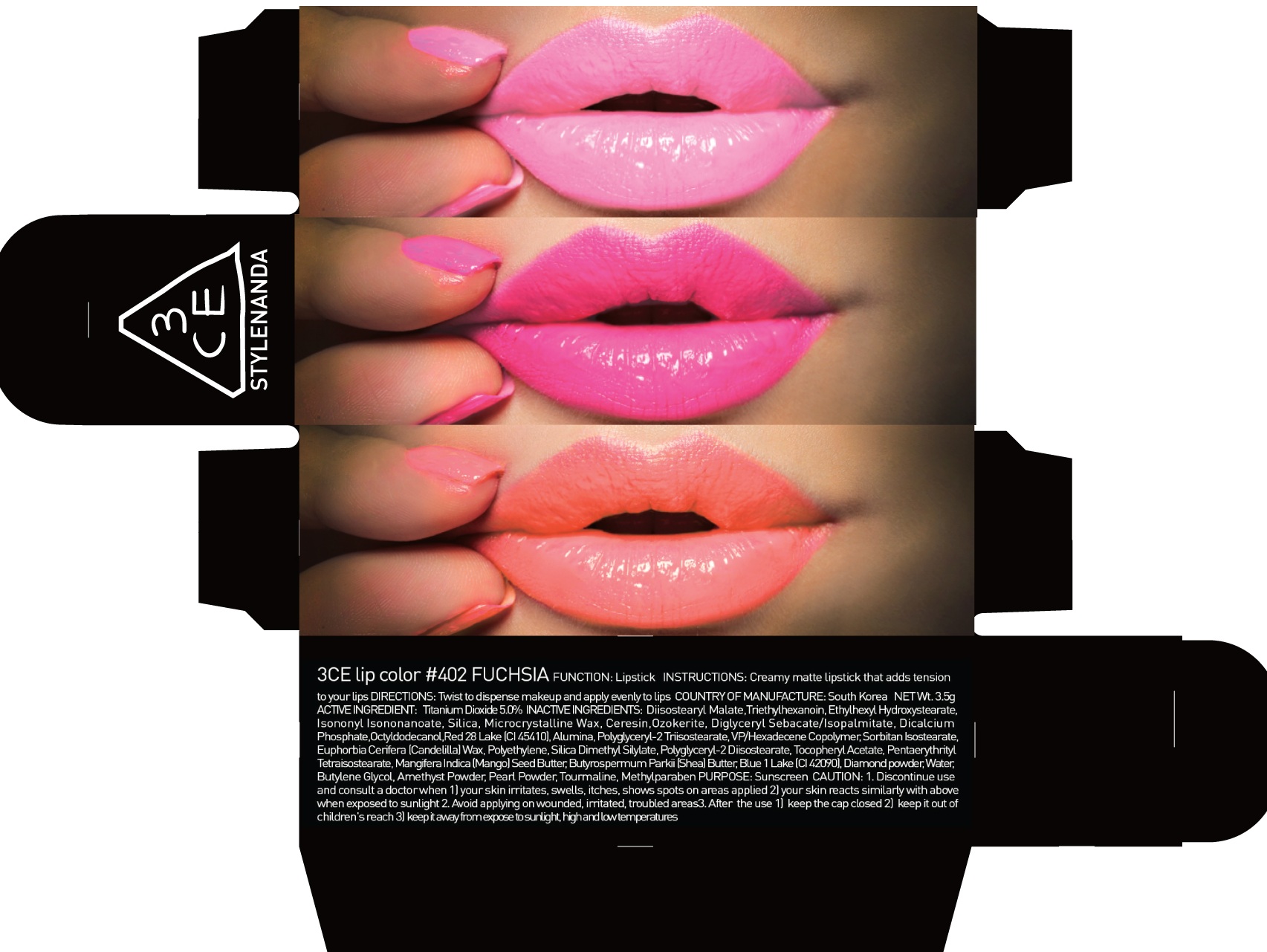 DRUG LABEL: 3CE LIP COLOR 402 FUCHSIA
NDC: 60764-070 | Form: LIPSTICK
Manufacturer: Nanda Co., Ltd
Category: otc | Type: HUMAN OTC DRUG LABEL
Date: 20161007

ACTIVE INGREDIENTS: Titanium Dioxide 0.17 g/3.5 g
INACTIVE INGREDIENTS: Triethylhexanoin; Diisostearyl Malate

ACTIVE INGREDIENT

Active Ingredient: Titanium Dioxide 5.0%

INACTIVE INGREDIENT

Inactive Ingredients: Triethylhexanoin, Diisostearyl Malate, Trimethylolpropane Tricaprylate/Tricaprate, Isononyl Isononanoate, Mica (CI 77019), Polyglyceryl-2 Triisostearate, Diglyceryl Sebacate/Isopalmitate, Silica, Ceresin, Ozokerite, Vinyl Dimethicone/Methicone Silsesquioxane Crosspolymer, Red 28 Lake (CI 45410), VP/Hexadecene Copolymer, Microcrystalline Wax, Sorbitan Isostearate, Silica Silylate, Polyethylene, Synthetic Wax, Silica Dimethyl Silylate, Polyglyceryl-2 Diisostearate, Methicone, Ethylene/Propylene Copolymer, Phytosteryl Macadamiate, Methylparaben, Mangifera Indica (Mango) Seed Butter, Butyrospermum Parkii (Shea) Butter, Water, Butylene Glycol, Diamond powder, Amethyst Powder, Pearl Powder, Tourmaline

PURPOSE

Purpose: Sunscreen

CAUTION

CAUTION: 1. Discontinue use and consult a doctor when - your skin irritates, swells, itches, shows spots on areas applied - your skin reacts similarly with above when exposed to sunlight 2. Avoid applying on wounded, irritated, troubled areas 3. After the use - keep the cap closed - keep it out of children's reach - keep it away from expose to sunlight, high and low temperatures

DESCRIPTION

INSTRUCTIONS: A rich color lipstick that moistly adheres to lips.

Directions: Twist to dispense makeup and apply evenly to lips